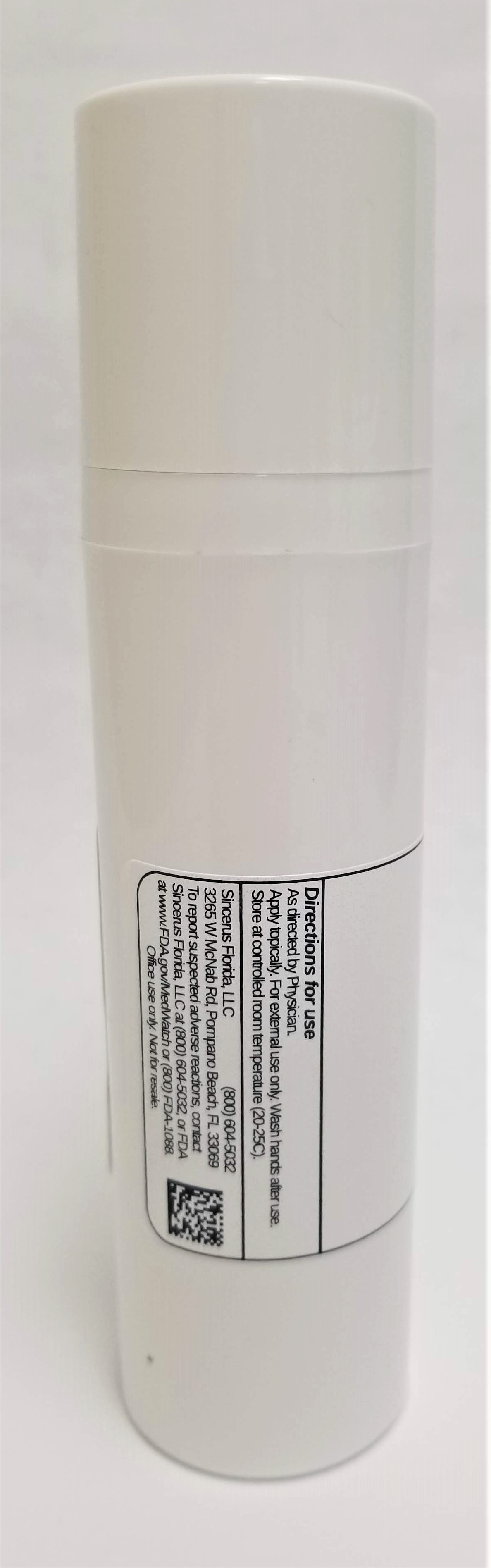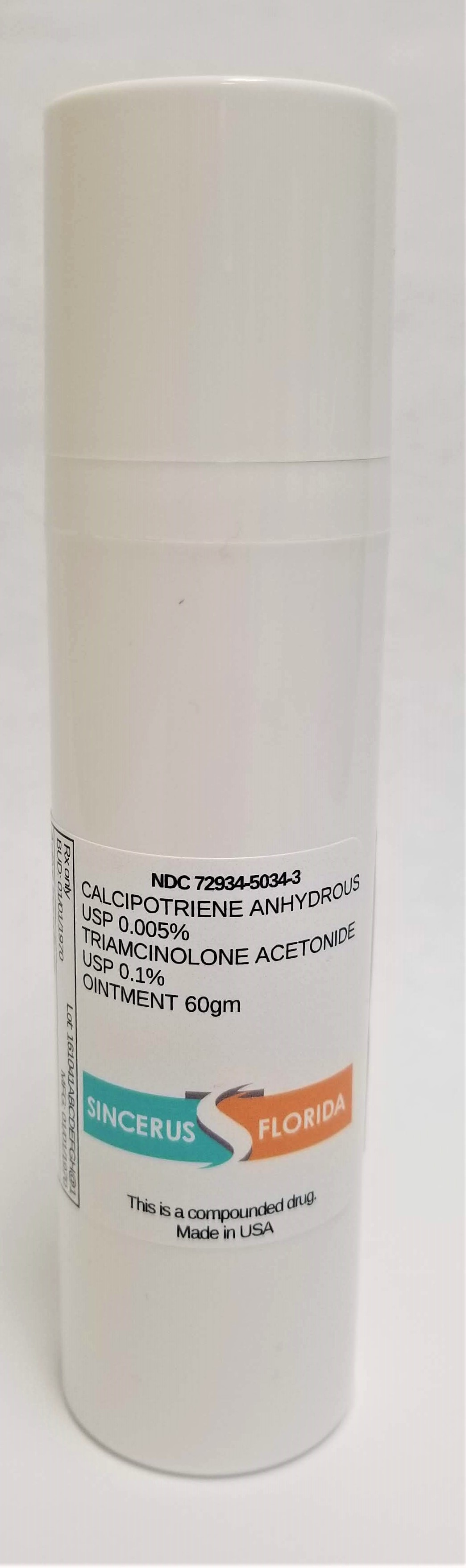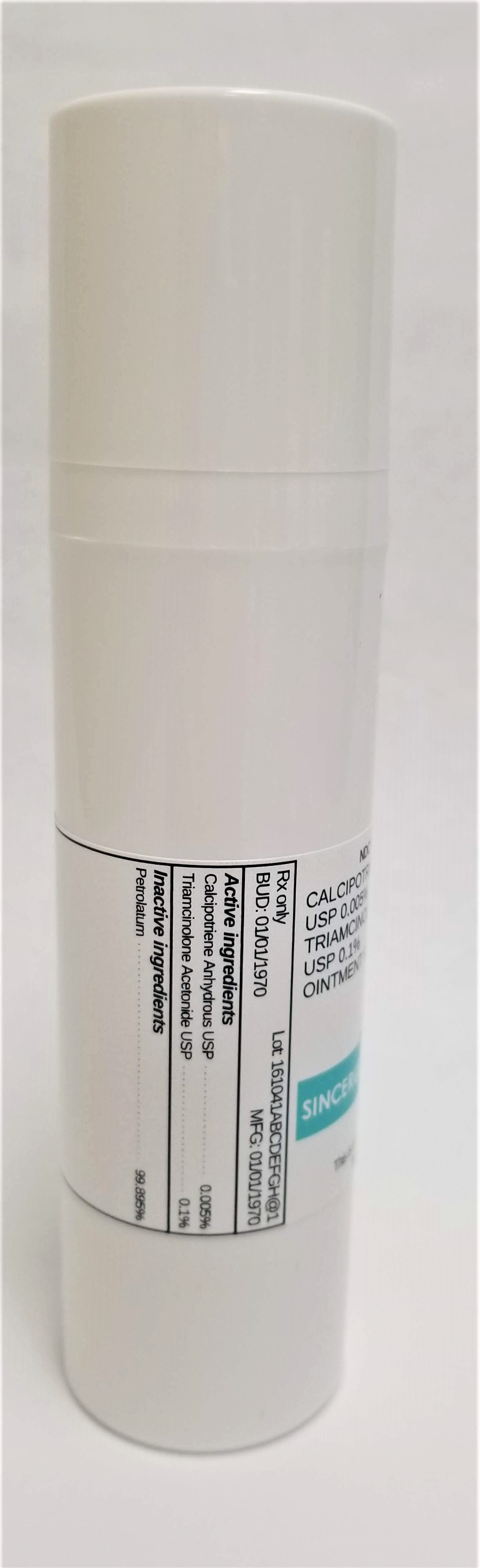 DRUG LABEL: CALCIPOTRIENE 0.005% / TRIAMCINOLONE ACETONIDE 0.1%
NDC: 72934-5034 | Form: OINTMENT
Manufacturer: Sincerus Florida, LLC
Category: prescription | Type: HUMAN PRESCRIPTION DRUG LABEL
Date: 20190510

ACTIVE INGREDIENTS: CALCIPOTRIENE 0.005 g/100 g; TRIAMCINOLONE ACETONIDE 0.1 g/100 g

CALCIPOTRIENE 0.005% / TRIAMCINOLONE ACETONIDE 0.1%